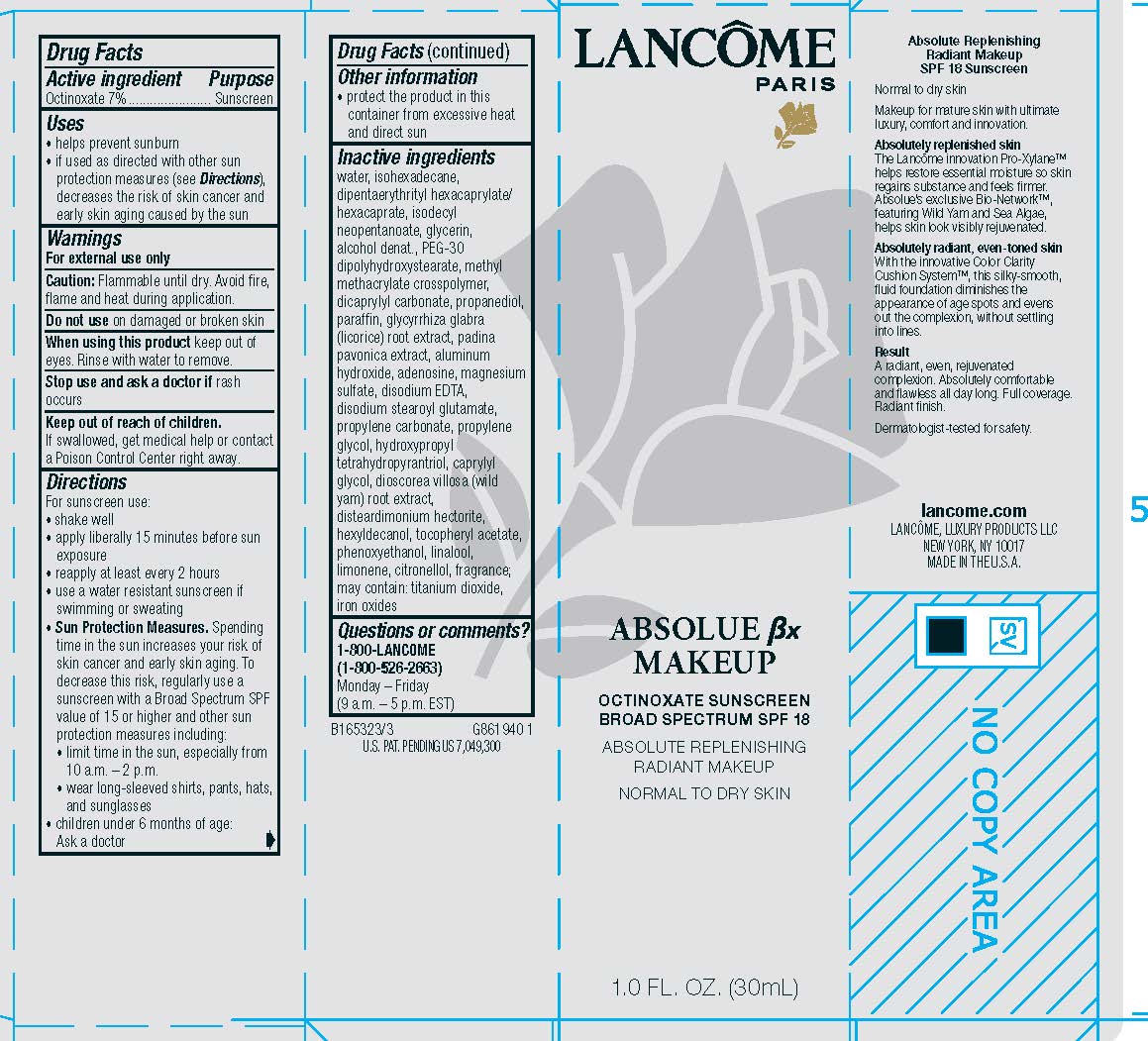 DRUG LABEL: Lancome Paris Absolue Bx Makeup Broad Spectrum SPF 18 Sunscreen Absolute Replenishing Radiant Makeup Normal to Dry Skin
NDC: 49967-439 | Form: LIQUID
Manufacturer: L'Oreal USA Products Inc
Category: otc | Type: HUMAN OTC DRUG LABEL
Date: 20231230

ACTIVE INGREDIENTS: OCTINOXATE 70 mg/1 mL
INACTIVE INGREDIENTS: WATER; ISOHEXADECANE; DIPENTAERYTHRITYL HEXACAPRYLATE/HEXACAPRATE; ISODECYL NEOPENTANOATE; GLYCERIN; ALCOHOL; PEG-30 DIPOLYHYDROXYSTEARATE; DICAPRYLYL CARBONATE; PROPANEDIOL; PARAFFIN; GLYCYRRHIZA GLABRA; PADINA PAVONICA; ALUMINUM HYDROXIDE; ADENOSINE; MAGNESIUM SULFATE, UNSPECIFIED FORM; EDETATE DISODIUM; DISODIUM STEAROYL GLUTAMATE; PROPYLENE CARBONATE; PROPYLENE GLYCOL; HYDROXYPROPYL TETRAHYDROPYRANTRIOL; CAPRYLYL GLYCOL; DIOSCOREA VILLOSA TUBER; DISTEARDIMONIUM HECTORITE; HEXYLDECANOL; .ALPHA.-TOCOPHEROL ACETATE; PHENOXYETHANOL; LINALOOL, (+/-)-; LIMONENE, (+)-; .BETA.-CITRONELLOL, (R)-; TITANIUM DIOXIDE; FERRIC OXIDE RED

Drug Facts

Active ingredient

Octinoxate 7%

Purpose

Sunscreen

Uses

- helps prevent sunburn
- if used as directed with other sun protection measures (see Directions), decreases the risk of skin cancer and early skin aging caused by the sun

Warnings

For external use only

Caution

Flammabile until dry. Avoid fire, flame and heat during application.

Do not use

on damaged or broken skin

When using this product

keep out of eyes. Rinse with water to remove.

Stop use and ask a doctor if

rash occurs

Keep out of reach of children.

If swallowed, get medical help or contact a Poison Control Center right away.

Directions

For sunscreen use:

● shake well

● apply liberally 15 minutes before sun exposure

● reapply at least every 2 hours

● use a water resistant sunscreen if swimming or sweating

● Sun Protection Measures. Spending time in the sun increases your risk of skin cancer and early skin aging. To decrease this risk, regularly use a sunscreen with a Broad Spectrum SPF value of 15 or higher and other sun protection measures including:

● limit time in the sun, especially from 10 a.m. – 2 p.m.

● wear long-sleeved shirts, pants, hats, and sunglasses

● children under 6 months of age: Ask a doctor

Other information

protect the product in this container from excessive heat and direct sun

Inactive ingredients

water, isohexadecane, dipentaerythrityl hexacaprylate/hexacaprate, isodecyl neopentanoate, glycerin, alcohol denat., PEG-30 dipolyhydroxystearate, methyl methacrylate crosspolymer, dicaprylyl carbonate, propanediol, paraffin, glycyrrhiza glabra (licorice) root extract, padina pavonica extract, aluminum hydroxide, adenosine, magnesium sulfate, disodium EDTA, disodium stearoyl glutamate, propylene carbonate, propylene glycol, hydroxypropyl tetrahydropyrantriol, caprylyl glycol, dioscorea villosa (wild yam) root extract, disteardimonium hectorite, hexyldecanol, tocopheryl acetate, phenoxyethanol, linalool, limonene, citronellol, fragrance; may conain: titanium dioxide, iron oxides

Questions or comments?

1-800-LANCOME

(1-800-526-2663)

Monday - Friday

(9 a.m. - 5 p.m. EST)